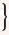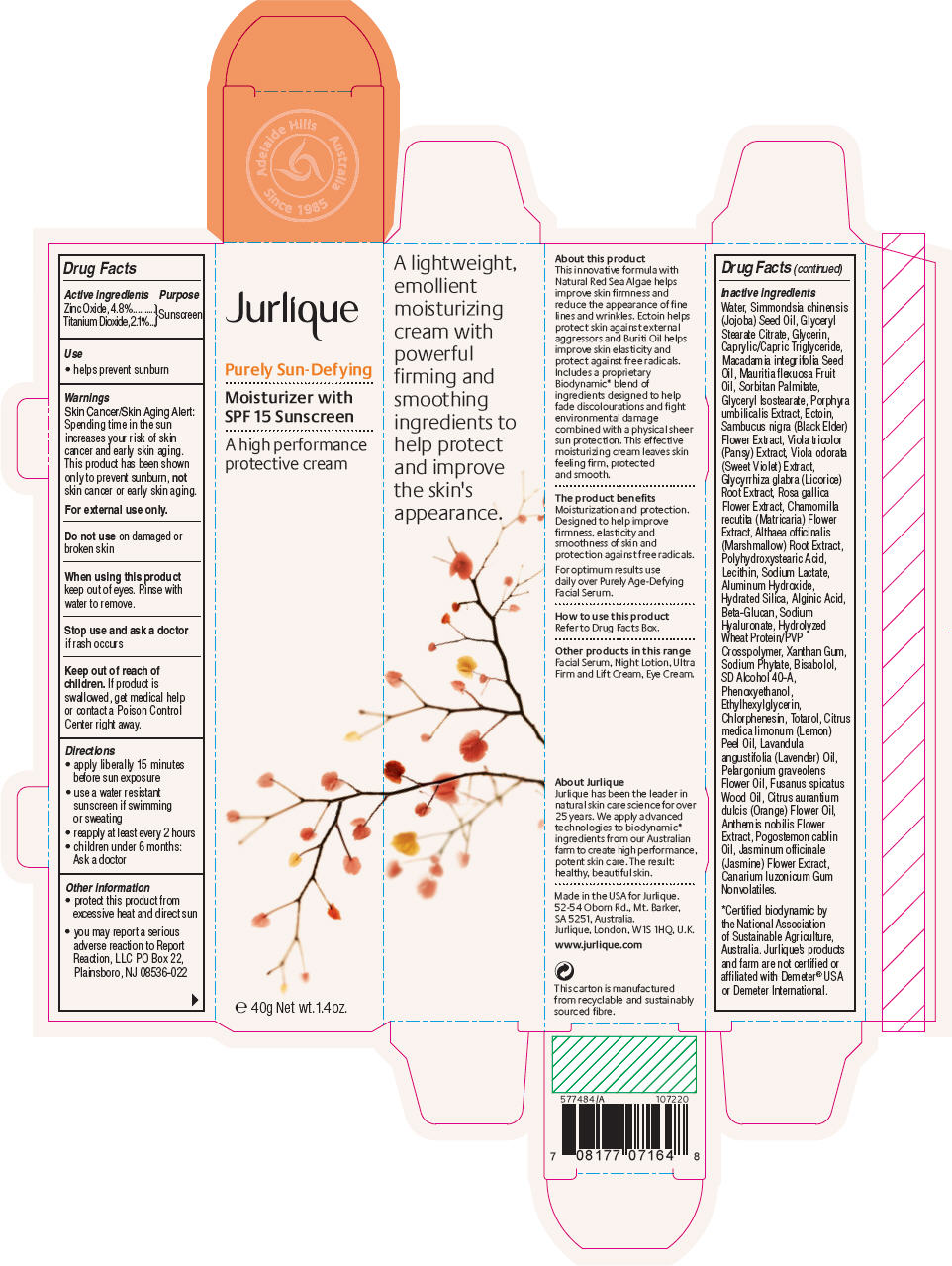 DRUG LABEL: Jurlique Purely Sun-Defying 
NDC: 68105-004 | Form: CREAM, AUGMENTED
Manufacturer: Jurlique International Pty. Ltd.
Category: otc | Type: HUMAN OTC DRUG LABEL
Date: 20110913

ACTIVE INGREDIENTS: ZINC OXIDE 4.8 g/100 g; TITANIUM DIOXIDE 2.1 g/100 g
INACTIVE INGREDIENTS: WATER; SIMMONDSIA CHINENSIS SEED; GLYCERYL STEARATE CITRATE; GLYCERIN; MEDIUM-CHAIN TRIGLYCERIDES; MACADAMIA OIL; MAURITIA FLEXUOSA FRUIT OIL; SORBITAN MONOPALMITATE; GLYCERYL ISOSTEARATE; POLYHYDROXYSTEARIC ACID (2300 MW); EGG PHOSPHOLIPIDS; ALCOHOL; SODIUM LACTATE; ALUMINUM HYDROXIDE; HYDRATED SILICA; ALGINIC ACID; SAMBUCUS NIGRA FLOWER; VIOLA TRICOLOR; VIOLA ODORATA; GLYCYRRHIZA GLABRA; ROSA GALLICA FLOWER; CHAMOMILE; ALTHAEA OFFICINALIS ROOT; HYALURONATE SODIUM; ECTOINE; XANTHAN GUM; LEVOMENOL; PHENOXYETHANOL; ETHYLHEXYLGLYCERIN; CHLORPHENESIN; LEMON OIL; LAVENDER OIL; PELARGONIUM GRAVEOLENS FLOWER OIL; SANTALUM SPICATUM OIL; CITRUS SINENSIS FLOWER OIL; CHAMAEMELUM NOBILE FLOWER; PATCHOULI OIL; JASMINUM OFFICINALE FLOWER; ELEMI

Jurlique
Purely Sun-Defying

Drug Facts

ACTIVE INGREDIENT

Active ingredients |  | Purpose
Zinc Oxide, 4.8% Titanium Dioxide, 2.1% |  | Sunscreen

Use

- helps prevent sunburn

Warnings

Skin Cancer/Skin Aging Alert

Spending time in the sun increases your risk of skin cancer and early skin aging. This product has been shown only to prevent sunburn, not skin cancer or early skin aging.

For external use only.

Do not use on damaged or broken skin

When using this product keep out of eyes. Rinse with water to remove.

Stop use and ask a doctor if rash occurs

Keep out of reach of children. If product is swallowed, get medical help or contact a Poison Control Center right away.

Directions

- apply liberally 15 minutes before sun exposure
- use a water resistant sunscreen if swimming or sweating
- reapply at least every 2 hours
- children under 6 months: Ask a doctor

Other information

- protect this product from excessive heat and direct sun
- you may report a serious adverse reaction to Report Reaction, LLC PO Box 22, Plainsboro, NJ 08536-022

Inactive ingredients

Water, Simmondsia chinensis (Jojoba) Seed Oil, Glyceryl Stearate Citrate, Glycerin, Caprylic/Capric Triglyceride, Macadamia integrifolia Seed Oil, Mauritia flexuosa Fruit Oil, Sorbitan Palmitate, Glyceryl Isostearate, Porphyra umbilicalis Extract, Ectoin, Sambucus nigra (Black Elder) Flower Extract, Viola tricolor (Pansy) Extract, Viola odorata (Sweet Violet) Extract, Glycyrrhiza glabra (Licorice) Root Extract, Rosa gallica Flower Extract, Chamomilla recutita (Matricaria) Flower Extract, Althaea officinalis (Marshmallow) Root Extract, Polyhydroxystearic Acid, Lecithin, Sodium Lactate, Aluminum Hydroxide, Hydrated Silica, Alginic Acid, Beta-Glucan, Sodium Hyaluronate, Hydrolyzed Wheat Protein/PVP Crosspolymer, Xanthan Gum, Sodium Phytate, Bisabolol, SD Alcohol 40-A, Phenoxyethanol, Ethylhexylglycerin, Chlorphenesin, Totarol, Citrus medica limonum (Lemon) Peel Oil, Lavandula angustifolia (Lavender) Oil, Pelargonium graveolens Flower Oil, Fusanus spicatus Wood Oil, Citrus aurantium dulcis (Orange) Flower Oil, Anthemis nobilis Flower Extract, Pogostemon cablin Oil, Jasminum officinale (Jasmine) Flower Extract, Canarium luzonicum Gum Nonvolatiles.

PRINCIPAL DISPLAY PANEL - 40g Tube Carton

Jurlique

Purely Sun-Defying

Moisturizer with
SPF 15 Sunscreen

A high performance
protective cream

e 40g Net wt. 1.4 oz.